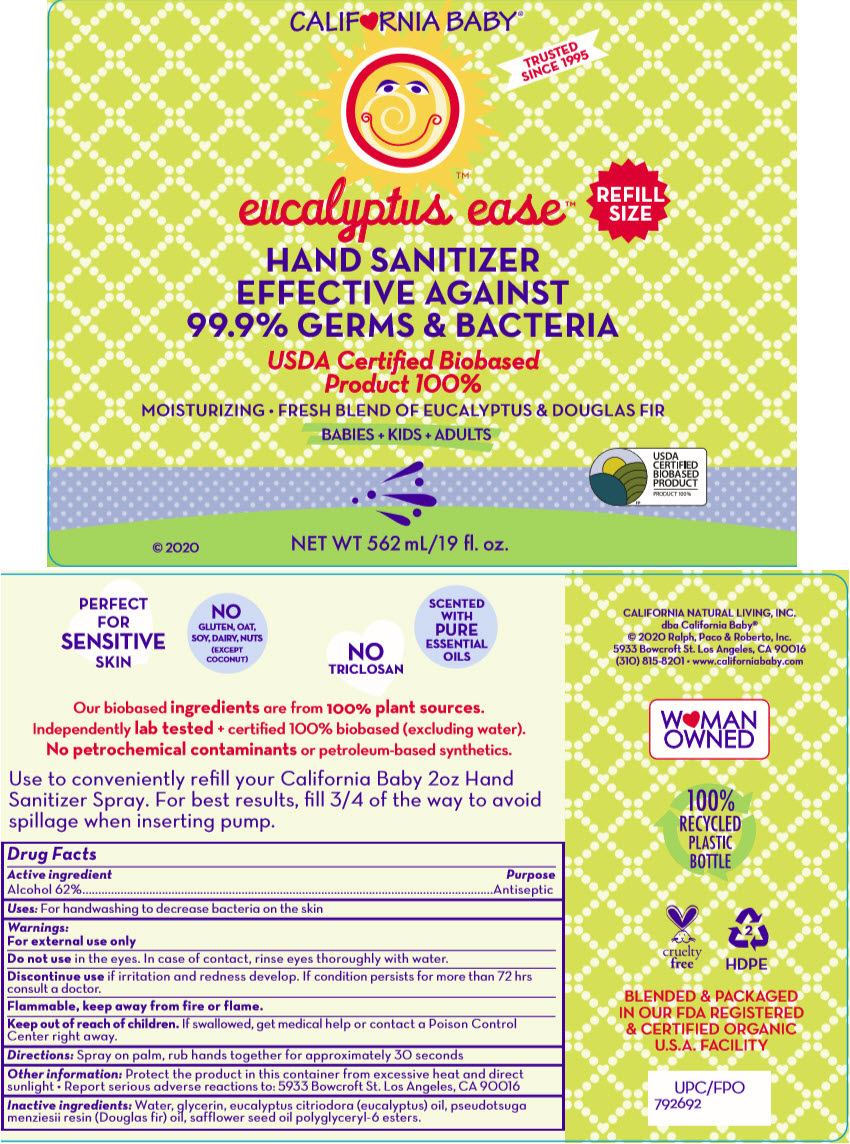 DRUG LABEL: EUCALYPTUS EASE HAND SANITIZER
NDC: 52915-075 | Form: SPRAY
Manufacturer: ORGANIC & SUSTAINABLE BEAUTY
Category: otc | Type: HUMAN OTC DRUG LABEL
Date: 20241106

ACTIVE INGREDIENTS: ALCOHOL 62 mL/100 mL
INACTIVE INGREDIENTS: WATER; GLYCERIN; CORYMBIA CITRIODORA LEAF OIL; PSEUDOTSUGA MENZIESII RESIN

EUCALYPTUS EASE™ HAND SANITIZER

Drug Facts

Active ingredient

Alcohol 62%

Purpose

Antiseptic

Uses

For handwashing to decrease bacteria on the skin

Warnings

For external use only

Do not use in the eyes. In case of contact, rinse eyes thoroughly with water.

Discontinue use if irritation and redness develop. If condition persists for more than 72 hrs consult a doctor.

Flammable, keep away from fire or flame.

Keep out of reach of children. If swallowed, get medical help or contact a Poison Control Center right away.

Directions

Spray on palm, rub hands together for approximately 30 seconds

Other information

Protect the product in this container from excessive heat and direct sunlight

- Report serious adverse reactions to: 5933 Bowcroft St. Los Angeles, CA 90016

Inactive ingredients

Water, glycerin, eucalyptus citriodora (eucalyptus) oil, pseudotsuga menziesii resin (Douglas fir) oil, safflower seed oil polyglyceryl-6 esters.

PRINCIPAL DISPLAY PANEL - 562 mL Spray Bottle Label

CALIF♥RNIA BABY®

TRUSTED
SINCE 1995

eucalyptus ease™

REFILL
SIZE

HAND SANITIZER
EFFECTIVE AGAINST
99.9% GERMS & BACTERIA

USDA Certiﬁed Biobased
Product 100%

MOISTURIZING • FRESH BLEND OF EUCALYPTUS & DOUGLAS FIR

BABIES + KIDS + ADULTS

© 2020

NET WT 562 mL/19 fl. oz.

USDA
CERTIFIED
BIOBASED
PRODUCT
PRODUCT 100%